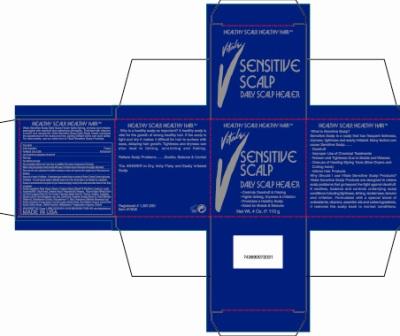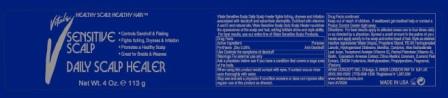 DRUG LABEL: Vitale Sensitive Scalp Daily Scalp Healer
NDC: 49681-001 | Form: CREAM
Manufacturer: New Life Products, Inc.
Category: otc | Type: HUMAN OTC DRUG LABEL
Date: 20210121

ACTIVE INGREDIENTS: PYRITHIONE ZINC 250 mg/100 g
INACTIVE INGREDIENTS: WATER; GLYCERIN; PROPYLENE GLYCOL; MINERAL OIL; LANOLIN; ACETIC MONOETHANOLAMIDE; CETYL ALCOHOL; CETOSTEARYL ALCOHOL; POLYSORBATE 60; YELLOW WAX; WHEAT GERM OIL; OLIVE OIL; JOJOBA OIL; MENTHOL, UNSPECIFIED FORM; CAMPHOR (SYNTHETIC); EUCALYPTUS OIL; ALOE VERA LEAF; DIMETHICONE; .ALPHA.-TOCOPHEROL ACETATE; VITAMIN A PALMITATE; STEARALKONIUM CHLORIDE; POLYQUATERNIUM-11 (1000000 MW); BIOTIN; ROSEMARY; EQUISETUM ARVENSE BRANCH; HOPS; LEMON PEEL; SODIUM BORATE; DMDM HYDANTOIN; METHYLPARABEN; PROPYLPARABEN

Active Ingredient

Pyrithione Zinc 0.25%

Purpose

Anti-Dandruff

Use

Controls the symptoms of dandruff

Warnings

For external use only

Ask a doctor before use if you have a condition that covers a large area of the body.

When using this product avoid contact with eyes. If contact occurs rinse eyes thoroughly with water.

Stop use and ask adoctor if condition worsens or dowes not improve after regular use of this product as directed.

Keep out of reach of children. If swallowed get medical help or contact a Poison Control Center right away.

Directions:

For best results apply to affected areas one to four times daily or as directed by a doctor. Spread a small amount in the palms of your hands and apply evenly to the scalp and entire head of hair. Style as desired.

Inactive ingredients

Water (Aqua), Glycerin, Propylene Glycol, Mineral Oil (Paraffinum Liquidum), Lanolin, Acetamide MEA, Cetyl Alcohol, Cetearyl Alcohol, Polysorbate 60, Beeswax, Triticum Vulgare (Wheat) Germ Oil, Olea Europaea (Olive) Oil, Simmondsia Chinensis (Jojoba) Seed Oil, Menthol, Camphor, Eucalyptus Globulus Leaf Oil, Aloe Barbadensis Leaf Juice, Dimethicone, Tocopherol Acetate (Vitamin E), Retinyl Palmitate (Vitamin A), Stearalkonium Chloride, Polyquaternium-11, Biotin, Rosmarinus Officinalis (Rosemary) Leaf Extract, Equisetum Arvense Extract, Humulus Lupulus (Hops) Extract, Citrus Medica Limonum, (Lemon) Peel Extract, Sodium Borate, DMDM Hydantoin, Methylparaben, Propylparaben, Fragrance, (Parfum)

AFAM CONCEPT, INC.
Chicago, IL 60629

London NW 10 6JH
UK

(800) 262-2326
(773) 838-1336

Registered # 1,387,930